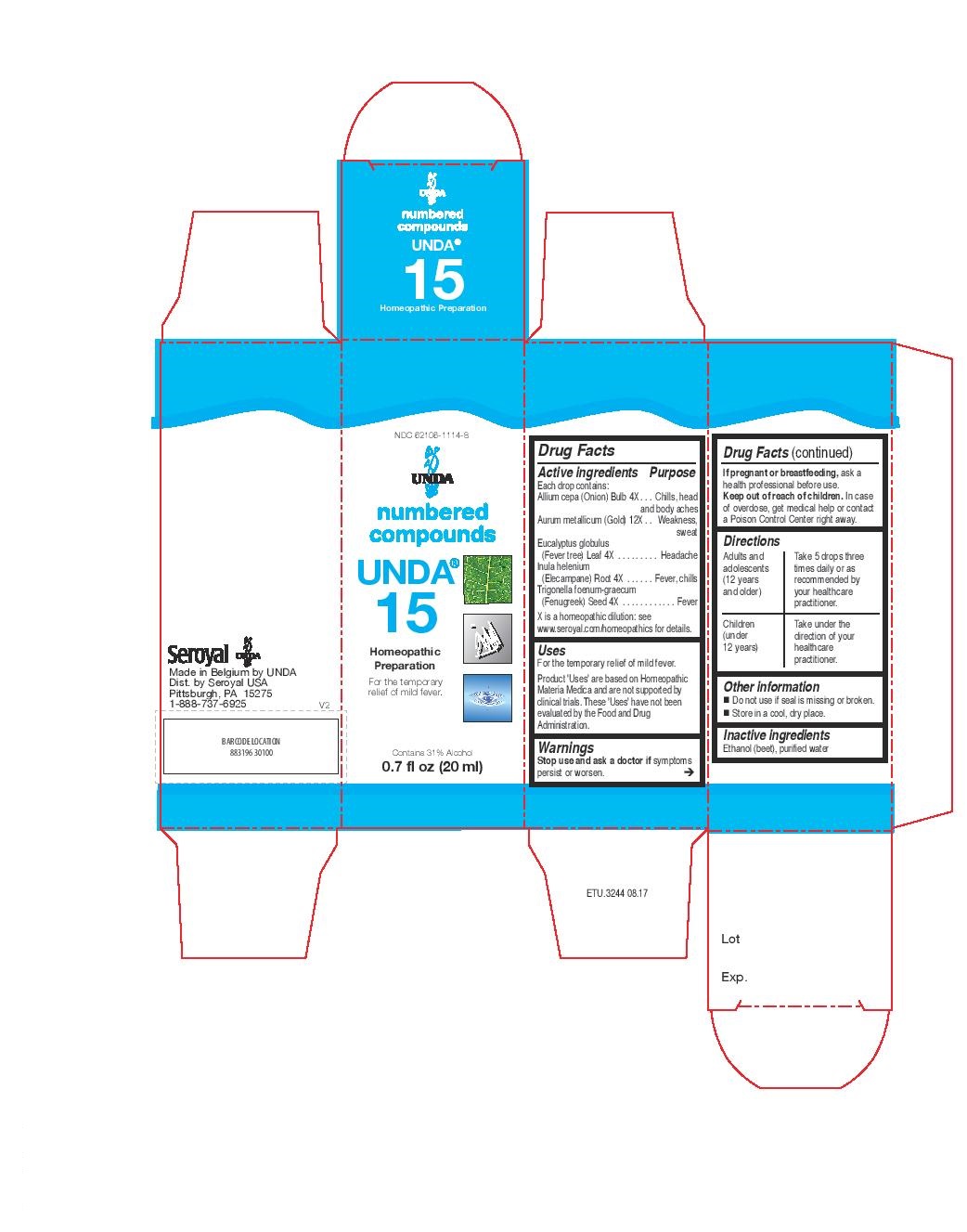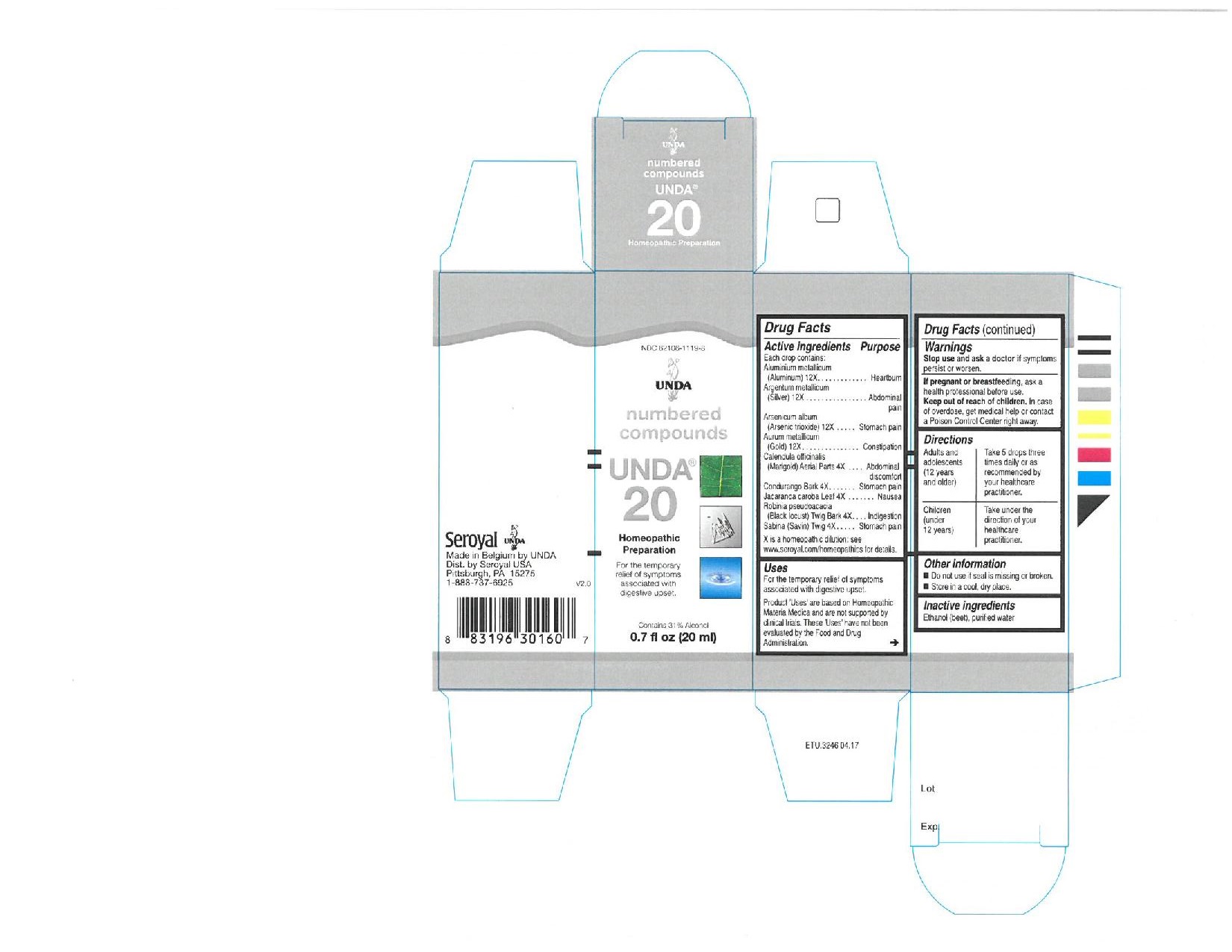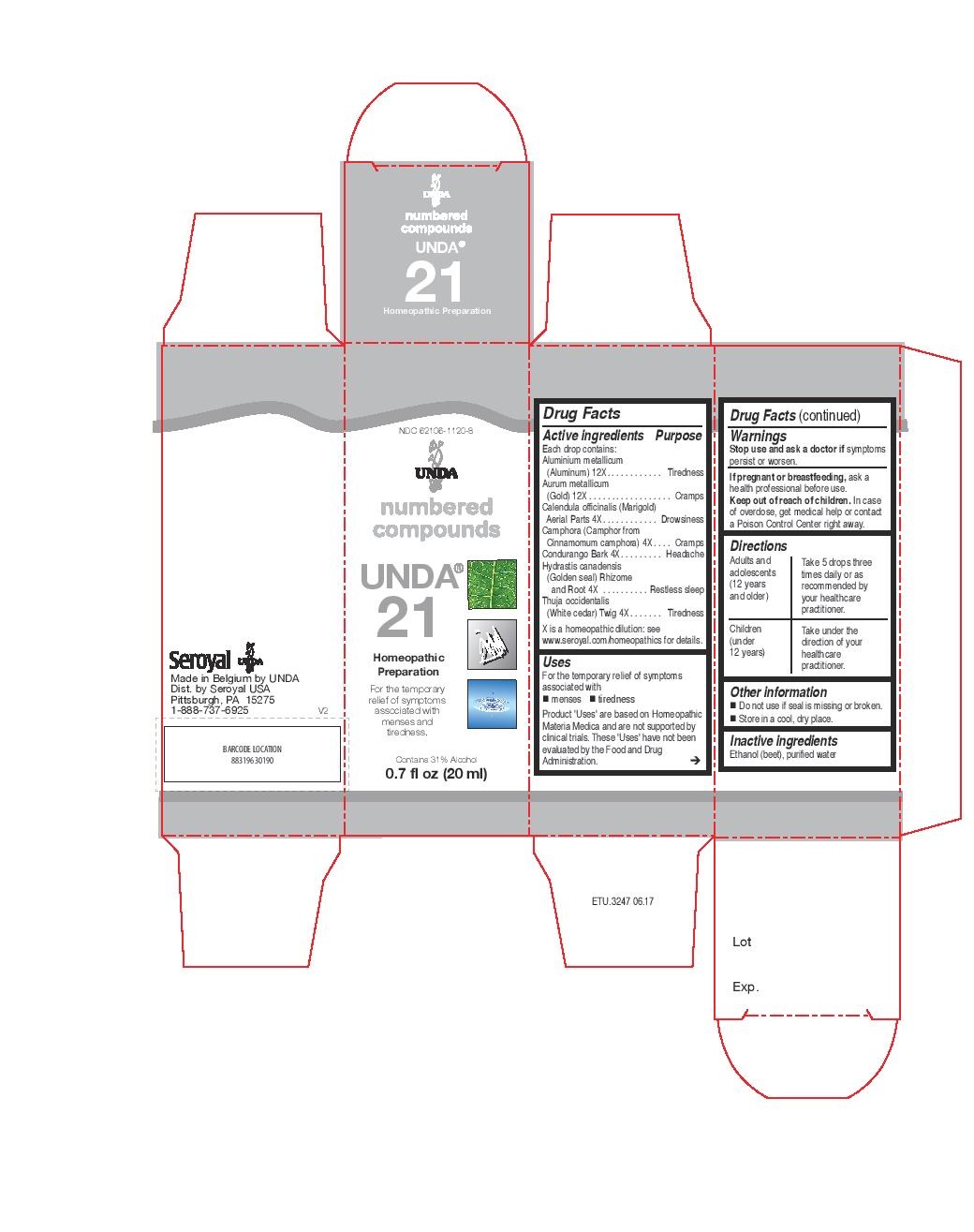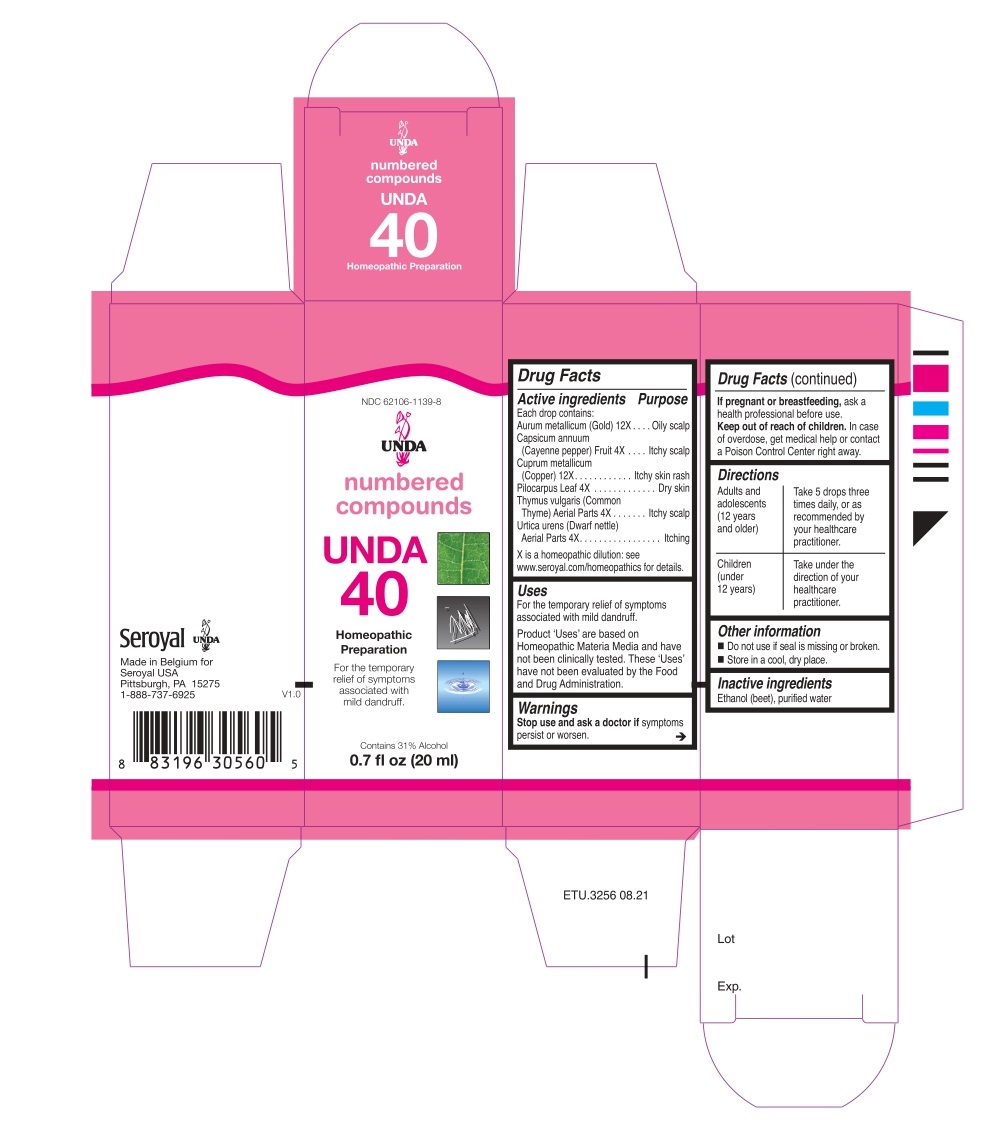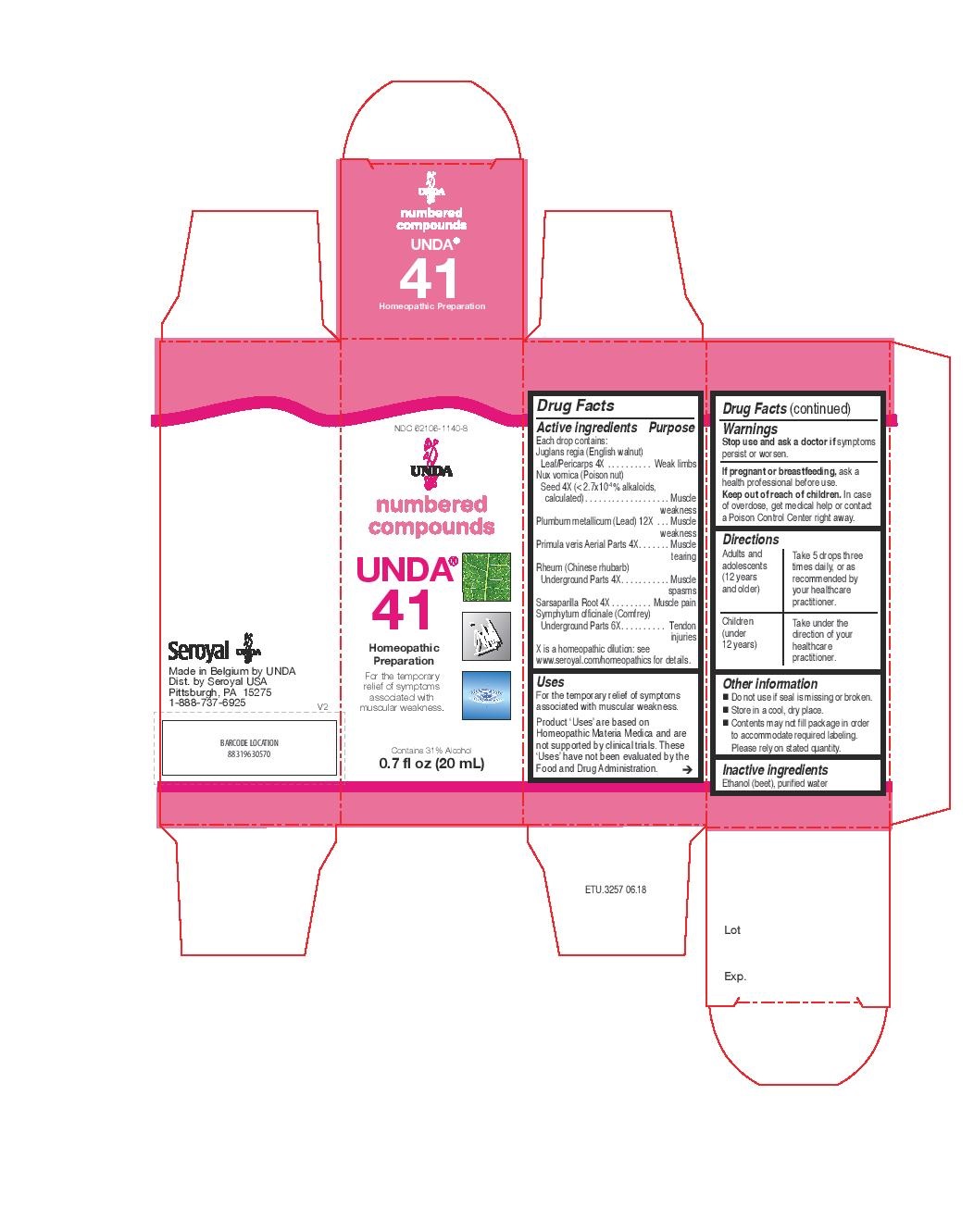 DRUG LABEL: UNDA 41
NDC: 62106-1140 | Form: LIQUID
Manufacturer: Seroyal USA
Category: homeopathic | Type: HUMAN OTC DRUG LABEL
Date: 20220428

ACTIVE INGREDIENTS: SARSAPARILLA 4 [hp_X]/20 mL; PRIMULA VERIS 4 [hp_X]/20 mL; STRYCHNOS NUX-VOMICA SEED 4 [hp_X]/20 mL; COMFREY ROOT 6 [hp_X]/20 mL; LEAD 12 [hp_X]/20 mL; RHEUM TANGUTICUM WHOLE 4 [hp_X]/20 mL; ENGLISH WALNUT 4 [hp_X]/20 mL
INACTIVE INGREDIENTS: ALCOHOL; WATER

UNDA Numbers

Active ingredients
Each drop contains:
Allium cepa (Onion) Bulb 4X
Aurum metallicum (Gold) 12X
Eucalyptus globulus (Fever tree) Leaf 4X
Inula helenium (Elecampane) Root 4X
Trigonella foenum-graecum (Fenugreek) Seed 4X

Uses
For the temporary relief of mild fever.

Warning:

Stop use and ask a doctor if symptoms persist or worsen.
If pregnant or breastfeeding, ask a health professional before use.
Keep out of reach of children.
In case of overdose, get medical help or contact a Poison Control Center right away.

PREGNANCY OR BREAST FEEDING

If pregnant or breastfeeding, ask a health professional before use.

Keep out of reach of children.

OVERDOSAGE

In case of overdose, get medical help or contact a Poison Control Center right away.

STOP USE

Stope use and aks a doctor if symptoms persist or worsen.

Other information

Do not use if seal is missing or broken.
Store in a cool, dry place.

Inactive Ingredients:

Ethanol (beet),
purified water

Directions
Adults and adolescents (12 years and older)

Take 5 drops three times daily or as recommended by your healthcare practitioner.

Children (under 12 years)

Take under the direction of your healthcare practitioner.

Uses

For the temporary relief of mild fever.

Directions
Adults and adolescents (12 years and older)

Take 5 drops three times daily or as recommended by your healthcare practitioner.

Children (under 12 years)

Take under the direction of your healthcare practitioner.

Active ingredients

Each drop contains equal parts of:
Aluminium metallicum (Aluminum) 12X
Argentum metallicum (Silver) 12X
Arsenicum album (Arsenic trioxide) 12X
Aurum metallicum (Gold) 12X
Calendula officinalis (Marigold) Flowering Tops 4X
Condurango Bark 4X
Jacaranda caroba Leaf 4X
Robinia pseudoacacia (Black locust) Twig Bark 4X
Sabina (Savin) Twig 4X

Uses
For the temporary relief of symptoms associated with digestive upset.

Warnings

Stop use and ask a doctor if symptoms persist or worsen.
If you are pregnant or breastfeeding, ask a health professional before use.
Keep out of reach of children.
In case of overdose, get medical help or contact a Poison Control Center right away.

PREGNANCY OR BREAST FEEDING

If you are pregnant or breastfeeding, ask a health professional before use.

Keep out of reach of children.

OVERDOSAGE

In case of overdose, get medical help or contact a Poison Control Center right away.

Stop use and ask a doctor if symptoms persist or worsen.

Other information
Do not use if seal is missing or broken.

Store in a cool, dry place.

Inactive Ingredients:

Ethanol (beet),
purified water

Directions
Adults and adolescents (12 years and older)

Take 5 drops three times daily or as recommended by your healthcare practitioner.

Children (under 12 years)

Take under the direction of your healthcare practitioner.

Uses
For the temporary relief of symptoms associated with digestive upset.

Directions

Adults and adolescents (12 years and older)

Take 5 drops three times daily or as recommended by your healthcare practitioner.

Children (under 12 years)

Take under the direction of your healthcare practitioner.

ACTIVE INGREDIENT

Each drop contains:
Aluminium metallicum (Aluminum) 12X
Aurum metallicum (Gold) 12X
Calendula officinalis (Marigold) Aerial Parts 4X
Camphora (Camphor from Cinnamomum camphora) 4X
Condurango Bark 4X
Hydrastis canadensis (Golden seal) Rhizome and Root 4X
Thuja occidentalis (White cedar) Twig 4X

Uses
For the temporary relief of symptoms associated with menses and tiredness

Warnings
Stop use and ask a doctor if symptoms persist or worsen.
If pregnant or breastfeeding, ask a health professional before use.
Keep out of reach of children. In case of overdose, get medical help or contact
a Poison Control Center right away.

PREGNANCY OR BREAST FEEDING

If pregnant or breastfeeding, ask a health professional before use.

Keep out of reach of children.

OVERDOSAGE

In case of overdose, get medical help or contact a Poison Control Center right away.

Stop use and ask a doctor if symptoms persist or worsen.

Inactive Ingredients:

Ethanol (beet),
purified water

Directions
Adults and adolescents (12 years and older)

Take 5 drops three times daily or as recommended by your healthcare practitioner.

Children (under 12 years)

Take under the direction of your healthcare practitioner.

Uses
For the temporary relief of symptoms associated with menses and tiredness

Directions
Adults and adolescents (12 years and older)

Take 5 drops three times daily or as recommended by your healthcare practitioner.

Children (under 12 years)

Take under the direction of your healthcare practitioner.

Active ingredients
Each drop contains:
Aurum metallicum (Gold) 12X
Capsicum annuum (Cayenne pepper) Fruit 4X
Cuprum metallicum (Copper) 12X
Pilocarpus Leaf 4X
Thymus vulgaris (Common Thyme) Aerial Parts 4X
Urtica urens (Dwarf nettle) Aerial Parts 4X

Uses
For the temporary relief of symptoms associated with mild dandruff.

Warnings
Stop use and ask a doctor if symptoms persist or worsen.

If pregnant or breastfeeding, ask a health professional before use.
Keep out of reach of children. In case of overdose, get medical help or contact
a Poison Control Center right away.

PREGNANCY OR BREAST FEEDING

If pregnant or breastfeeding, ask a health professional before use.

Keep out of reach of children.

OVERDOSAGE

In case of overdose, get medical help or contact a Poison Control Center right away.

Stop use and ask a doctor if symptoms persist or worsen.

Other information
Do not use if seal is missing or broken.
Store in a cool, dry place.

Inactive ingredients
Ethanol (beet), purified water

Directions
Adults and adolescents (12 years and older)

Take 5 drops three times daily, or as recommended by your healthcare practitioner.
Children (under 12 years)
Take under the direction of your healthcare practitioner.

Uses
For the temporary relief of symptoms associated with mild dandruff.

Directions
Adults and adolescents (12 years and older)

Take 5 drops three times daily, or as recommended by your healthcare practitioner.
Children (under 12 years)
Take under the direction of your healthcare practitioner.

Active ingredients

Each Drop Contains:

Primula veris Whole Plant . 4X
Rheum (Chinese rhubarb) Underground Parts . 4X
Juglans regia (English walnut) Leaf/Rind/Unripe Fruit . 4X
Sarsaparilla Root . 4X
Nux vomica (Poison nut) Seed . 4X
Symphytum officinale (Comfrey) Root . 6X
Plumbum metallicum (Lead). 12X

Uses
For the relief of symptoms associated with muscular
weakness in the elderly.

Warnings
If you are pregnant or breastfeeding, ask a healthcare practitioner before use.
Keep out of reach of children.
In case of overdose, get medical help or contact a Poison Control Center right away.
Stop use and ask a doctor if symptoms persist or worsen.

PREGNANCY OR BREAST FEEDING

If you are pregnant or breastfeeding, ask a healthcare practitioner before use.

Keep out of reach of children.

OVERDOSAGE

In case of overdose, get medical help or contact a Poison Control Center right away.

Stop use and ask a doctor if symptoms persist or worsen.

Inactive Ingredients:

Ethanol (beet),
purified water

Directions

Adults and adolescents (12 years and older)

Take 5 drops three times daily, or as recommended by your healthcare practitioner.

Children (under 12 years)

Take under the direction of your healthcare practitioner.

Uses
For the relief of symptoms associated with muscular
weakness in the elderly.

Directions

Adults and adolescents (12 years and older)

Take 5 drops three times daily, or as recommended by your healthcare practitioner.

Children (under 12 years)

Take under the direction of your healthcare practitioner.

PACKAGE LABEL

NDC 62106-1139-8

UNDA

numbered compounds

UNDA 40

Homeopathic Preparation

For the temporary relief of symptoms
associated with mild dandruff.

Contains 31% Alcohol
0.7 fl oz (20 ml)

PACKAGE LABEL

NDC 62106-1114-8

UNDA

numbered compounds

UNDA 15

Homeopathic Preparation

For the temporary relief of mild fever.

Contains 31% Alcohol
0.7 fl oz (20 ml)

PACKAGE LABEL

NDC 62106-1120-8

UNDA

numbered compounds

UNDA 21

Homeopathic Preparation

For the temporary relief of symptoms
associated with menses and tiredness.

Contains 31% Alcohol
0.7 fl oz (20 ml)

PACKAGE LABEL

NDC 62106-1119-8

UNDA

numbered compounds

UNDA 20

Homeopathic Preparation

For the temporary relief of symptoms

associated with digestive upset.

Contains 31% Alcohol
0.7 fl oz (20 ml)

PACKAGE LABEL

NDC 62106-1140-8

UNDA

numbered compounds

UNDA 41

Homeopathic Preparation

For the temporary relief of symptoms
associated with muscular weakness.

Contains 31% Alcohol
0.7 fl oz (20 mL)